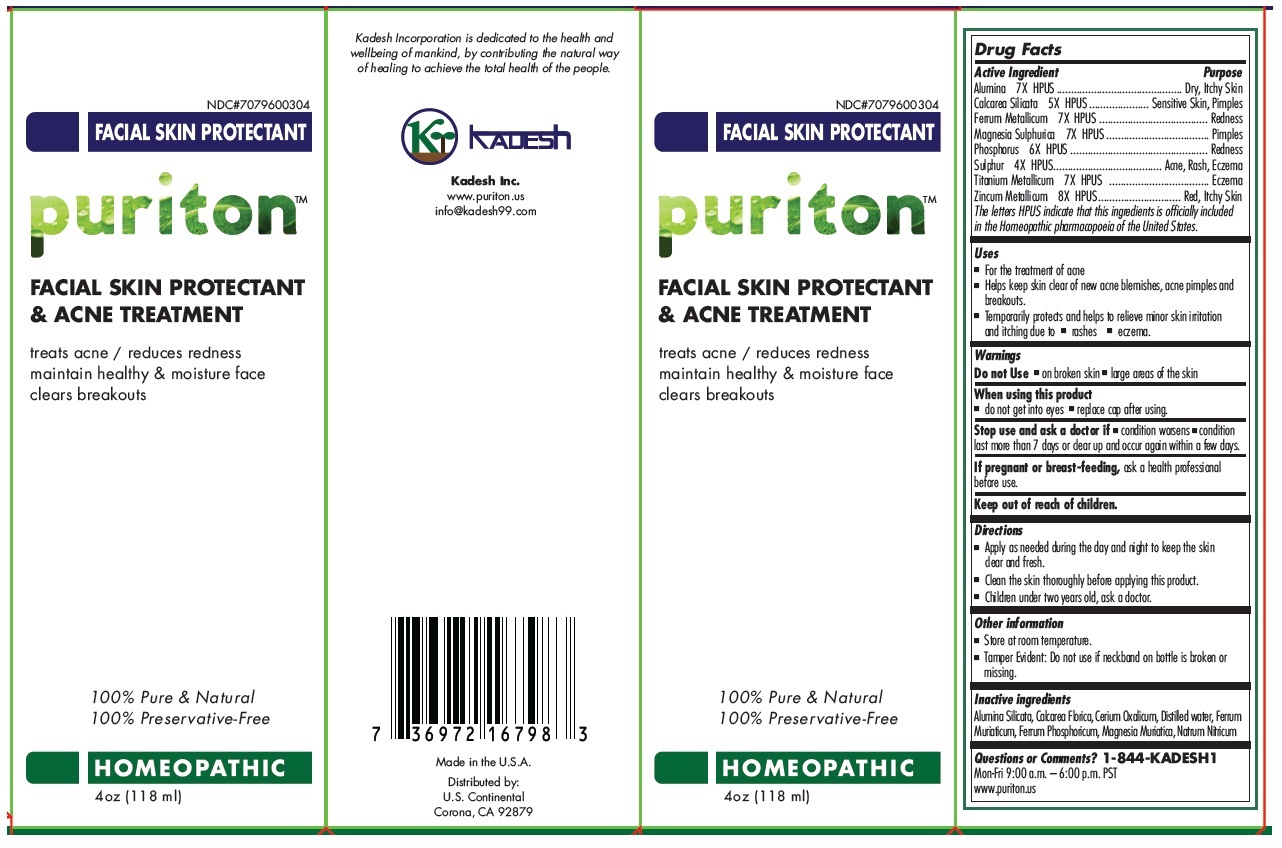 DRUG LABEL: Puriton FACIAL SKIN PROTECTANT AND ACNE TREATMENT HOMEOPATHIC
NDC: 70796-003 | Form: SOLUTION
Manufacturer: Kadesh, Inc.
Category: homeopathic | Type: HUMAN OTC DRUG LABEL
Date: 20160803

ACTIVE INGREDIENTS: ALUMINUM OXIDE 7 [hp_X]/118 mL; CALCIUM SILICATE 5 [hp_X]/118 mL; IRON 7 [hp_X]/118 mL; MAGNESIUM SULFATE HEPTAHYDRATE 7 [hp_X]/118 mL; PHOSPHORUS 6 [hp_X]/118 mL; SULFUR 4 [hp_X]/118 mL; TITANIUM 7 [hp_X]/118 mL; ZINC 8 [hp_X]/118 mL
INACTIVE INGREDIENTS: KAOLIN; CALCIUM FLUORIDE; CEROUS OXALATE NONAHYDRATE; WATER; FERRIC CHLORIDE HEXAHYDRATE; FERROSOFERRIC PHOSPHATE; MAGNESIUM CHLORIDE; SODIUM NITRATE

puriton FACIAL SKIN PROTECTANT AND ACNE TREATMENT HOMEOPATHIC

Active ingredients

Alumina 7X HPUS
Calcarea Silicata 5X HPUS
Ferrum Metallicum 7X HPUS
Magnesia Sulphurica 7X HPUS
Phosphorous 6X HPUS
Sulphur 4X HPUS
Titanium Metallicum 7X HPUS
Zincum Metallicum 8X HPUS

The letters HPUS indicate that this ingredients is officially included in the Homoeopathic pharmacopoeia of the United States

Purpose

Dry, Itchy Skin
Sensitive Skin, Pimples
Redness
Pimples
Redness
Acne, Rash, Eczema
Eczema
Red, Itchy Skin

Uses

• For the treatment of acne
• Helps keep skin clear of new acne blemishes, acne pimples and breakouts.
• Temporarily protects and helps to relieve minor skin irritation and itching due to • rashes • eczema

Warnings

Do not Use • on broken skin • large areas of the skin

When using this product

• do not get into eyes • replace cap after using

Stop use and ask a doctor if • condition worsens • condition last more than 7 days or clear up and occur again within a few days.

If pregnant or breast-feeding, ask a health professional before use.

Keep out of reach of children

Directions

• Apply as needed during the day and night to keep the skin clear and fresh.
• Clean the skin thoroughly before applying this product
• Children under two years old : ask a doctor

Inactive ingredients

Alumina Silicata, Calcarea Fluorica, Cerium Oxalicum, Distilled Water, Ferrum Muriaticum, Ferrum Phosphoricum, Magnesia Muriatica, Natrum Nitricum

Other information

• Store at room temperature.
• Tamper Evident: Do not use if neckband on bottle is broken or missing.

Questions or Comments? 1-844-KADESH1
Mon - Fri 9.00 a.m. - 6.00 p.m. PST
www.puriton.us

treats acne / reduces redness

maintain healthy & moisture face

clears breakouts

100% Pure & Natural

100% Preservative-Free

Made in the U.S.A

Distributed by:
U.S. Continental

Corona, CA 92879

info@kadesh99.com